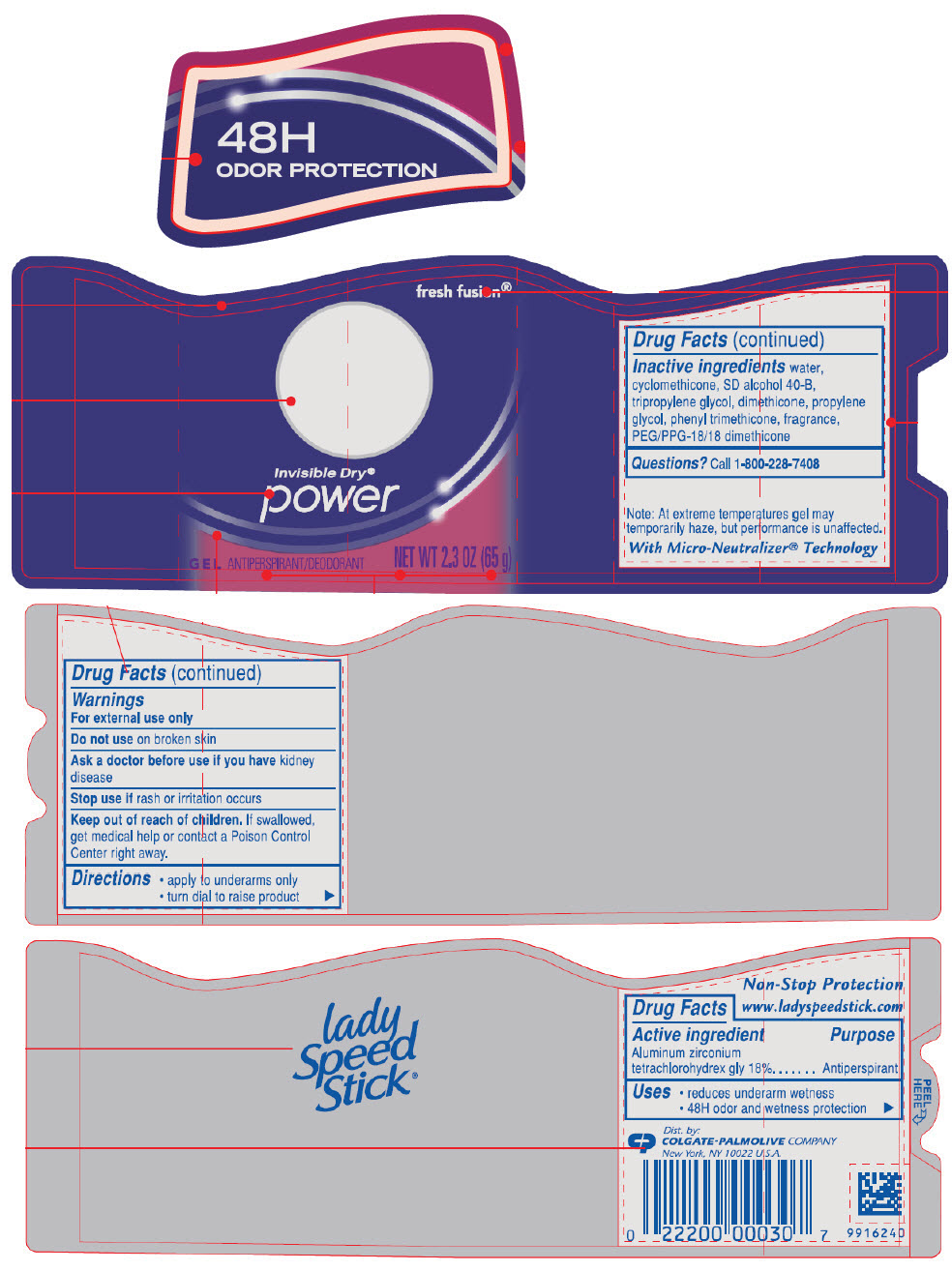 DRUG LABEL: Lady Speed Stick
NDC: 35000-855 | Form: STICK
Manufacturer: COLGATE PALMOLIVE COMPANY
Category: otc | Type: HUMAN OTC DRUG LABEL
Date: 20210519

ACTIVE INGREDIENTS: ALUMINUM ZIRCONIUM TETRACHLOROHYDREX GLY 180 mg/1 g
INACTIVE INGREDIENTS: WATER; CYCLOMETHICONE; ALCOHOL; TRIPROPYLENE GLYCOL; DIMETHICONE; PROPYLENE GLYCOL; PHENYL TRIMETHICONE; PEG/PPG-18/18 DIMETHICONE

lady
Speed
Stick®
fresh
fusion®

Drug Facts

Active ingredient

Aluminum zirconium tetrachlorohydrex gly 18%

Purpose

Antiperspirant

Uses

- reduces underarm wetness
- lasts all day

Warnings

For external use only

Do not use on broken skin

Ask a doctor before use if you have kidney disease

Stop use if rash or irritation occurs

Keep out of reach of children. If swallowed, get medical help or contact a Poison Control Center right away.

Directions

- apply to underarms only
- turn dial to raise product

Inactive ingredients

water, cyclomethicone, SD alcohol 40-B, tripropylene glycol, dimethicone, propylene glycol, phenyl trimethicone, fragrance, PEG/PPG-18/18 dimethicone

Questions?

Call toll-free 1-800-228-7408

Dist. by:
COLGATE-PALMOLIVE COMPANY
New York, NY 10022

PRINCIPAL DISPLAY PANEL - 65 g Container Label

48H
ODOR PROTECTION

fresh fusion®

Invisible Dry®
power

GEL ANTIPERSPIRANT/DEODORANT

NET WT 2.3 OZ (65 g)